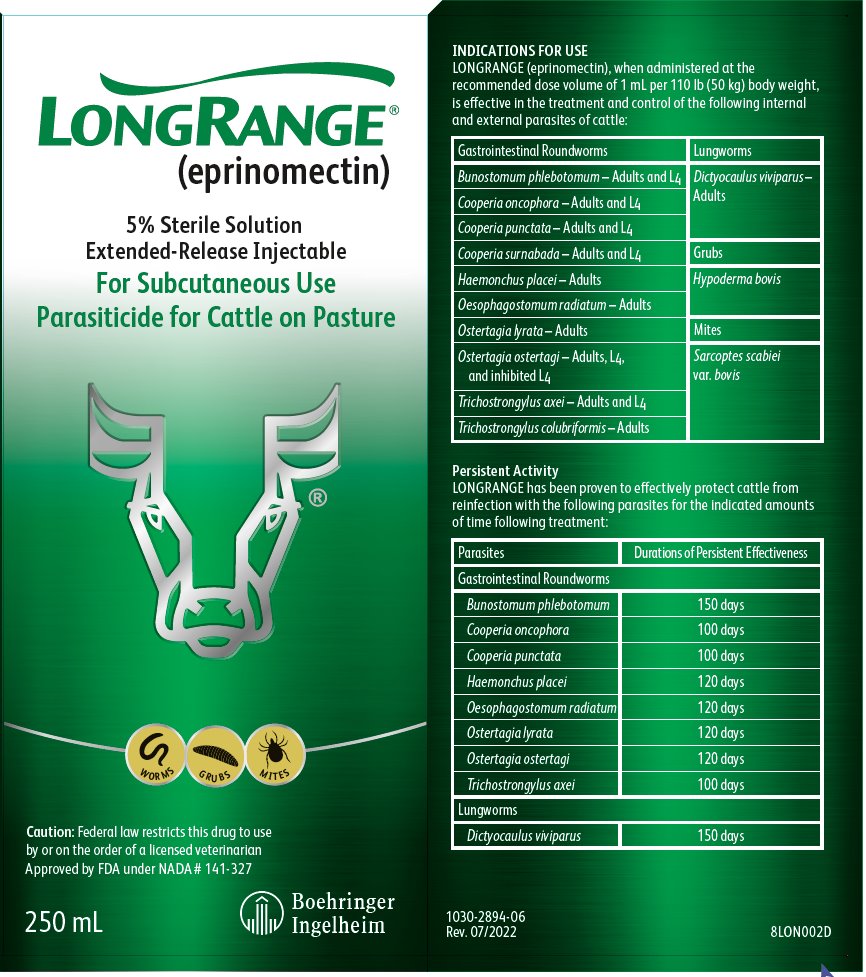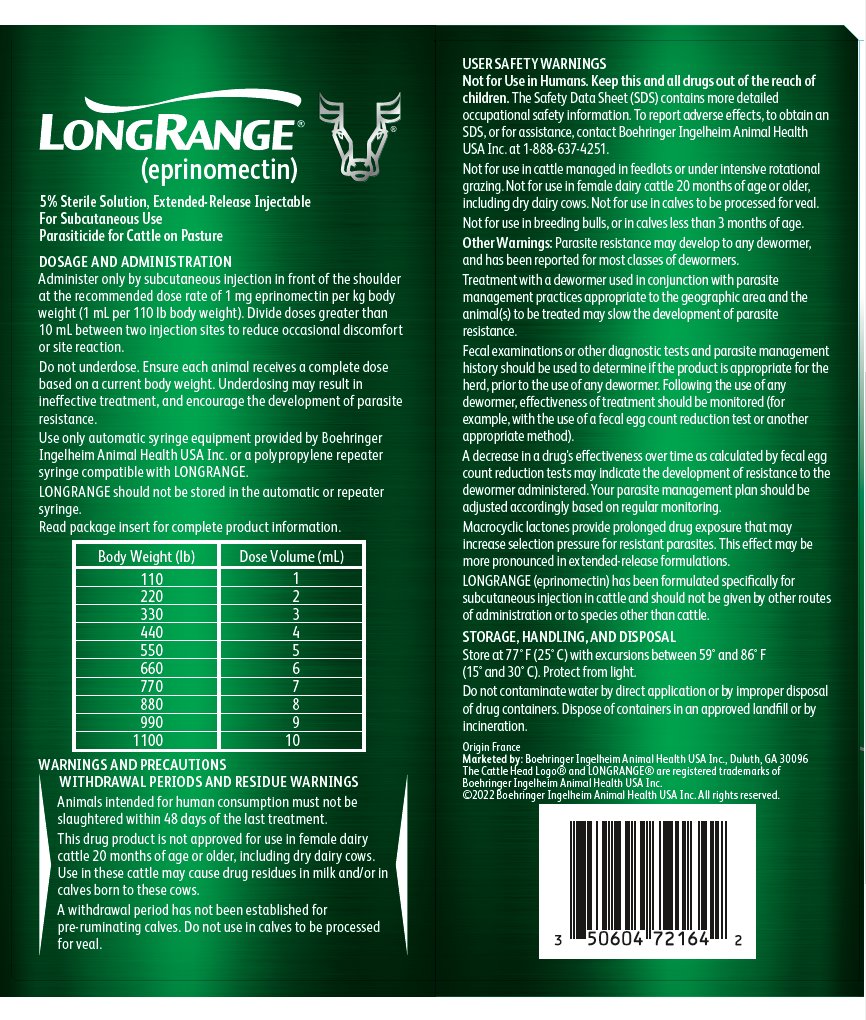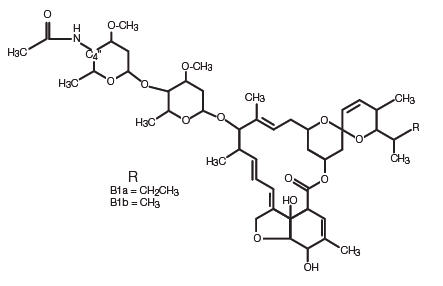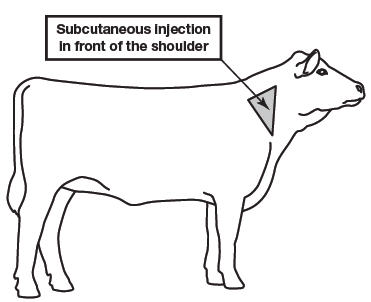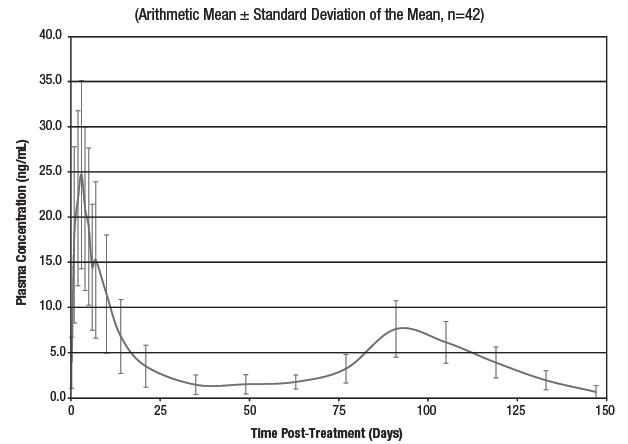 DRUG LABEL: LongRange
NDC: 0010-7216 | Form: INJECTION, SOLUTION
Manufacturer: Boehringer Ingelheim Animal Health USA Inc.
Category: animal | Type: PRESCRIPTION ANIMAL DRUG LABEL
Date: 20231220

ACTIVE INGREDIENTS: eprinomectin 50 mg/1 mL
INACTIVE INGREDIENTS: methylpyrrolidone; triacetin; butylated hydroxytoluene

LONGRANGE®
(eprinomectin)

VETERINARY INDICATIONS

5% Sterile Solution

Extended-Release Injectable

For Subcutaneous Use Parasiticide for Cattle on Pasture

For the Treatment and Control of Internal and External Parasites of Cattle on Pasture with Persistent Effectiveness

Not for use in female dairy cattle 20 months of age or older, including dry dairy cows. Not for use in calves to be processed for veal.

Not for use in breeding bulls, or in calves less than 3 months of age.

Not for use in cattle managed in feedlots or under intensive rotational grazing.

Caution: Federal law restricts this drug to use by or on the order of a licensed veterinarian.

DESCRIPTION

LONGRANGE (eprinomectin) is a ready-to-use, sterile injectable preparation containing eprinomectin, a member of the macrocyclic lactone class of antiparasitics. Each mL of LONGRANGE contains 50 mg of eprinomectin in a co-solvent system of N-methyl-2-pyrrolidone (30% v/v) and triacetin (qs), along with 50 mg of poly-lactide-co-glycolic-acid 75:25 (PLGA), a polymer that allows a slow release of eprinomectin from the formulation, thereby maintaining a prolonged duration of product effectiveness. Butylated hydroxytoluene (0.2 mg/mL) acts as an antioxidant in the formulation.

The chemical name of eprinomectin is 4"-deoxy-4"-epiacetylamino-avermectin B1. It is a semi-synthetic member of the avermectin family of compounds consisting of a mixture of two homologous components, B1a and B1b, which differ by a single methylene group at C26.

INDICATIONS FOR USE

LONGRANGE, when administered at the recommended dose volume of 1 mL per 110 lb (50 kg) body weight, is effective in the treatment and control of the following internal and external parasites of cattle:

Gastrointestinal Roundworms | Lungworms
Bunostomum phlebotomum – Adults and L4 | Dictyocaulus viviparus – Adults
Cooperia oncophora – Adults and L4 | Dictyocaulus viviparus – Adults
Cooperia punctata – Adults and L4 | Dictyocaulus viviparus – Adults
Cooperia surnabada – Adults and L4 | Grubs
Haemonchus placei – Adults | Hypoderma bovis
Oesophagostomum radiatum – Adults
Ostertagia lyrata – Adults | Mites
Ostertagia ostertagi – Adults, L4, and inhibited L4 | Sarcoptes scabiei var. bovis
Trichostrongylus axei – Adults and L4
Trichostrongylus colubriformis – Adults

Persistent Activity

LONGRANGE has been proven to effectively protect cattle from reinfection with the following parasites for the indicated amounts of time following treatment:

Parasites | Durations of Persistent Effectiveness
Gastrointestinal Roundworms
Bunostomum phlebotomum | 150 days
Cooperia oncophora | 100 days
Cooperia punctata | 100 days
Haemonchus placei | 120 days
Oesophagostomum radiatum | 120 days
Ostertagia lyrata | 120 days
Ostertagia ostertagi | 120 days
Trichostrongylus axei | 100 days
Lungworms
Dictyocaulus viviparus | 150 days

DOSAGE AND ADMINISTRATION

LONGRANGE (eprinomectin) should be given only by subcutaneous injection in front of the shoulder at the recommended dosage level of 1 mg eprinomectin per kg body weight (1 mL per 110 lb body weight).

Each mL of LONGRANGE contains 50 mg of eprinomectin, sufficient to treat 110 lb (50 kg) body weight. Divide doses greater than 10 mL between two injection sites to reduce occasional discomfort or site reaction.

Do not underdose. Ensure each animal receives a complete dose based on a current body weight. Underdosing may result in ineffective treatment, and encourage the development of parasite resistance.

Body Weight (lb) | Dose Volume (mL)
110 | 1
220 | 2
330 | 3
440 | 4
550 | 5
660 | 6
770 | 7
880 | 8
990 | 9
1100 | 10

LONGRANGE is to be given subcutaneously only. Animals should be appropriately restrained to achieve the proper route of administration. Inject under the loose skin in front of the shoulder (see illustration) using a 16 or 18 gauge, ½ to ¾ inch needle.

Sanitize the injection site by applying a suitable disinfectant. Clean, properly disinfected needles should be used to reduce the potential for injection site infections.

100 mL bottle size: Use only polypropylene syringes. Not for use with polycarbonate syringe material. If syringe material is not known, contact the syringe manufacturer prior to use for identification. Alternatively, a 50-mL polypropylene repeater syringe compatible with LONGRANGE may be used. To obtain a list of compatible equipment, contact Boehringer Ingelheim Animal Health USA Inc. at 1-888-637-4251. Do not use beyond 3 months after stopper has been punctured. Discard bottle after 15 stopper punctures. LONGRANGE should not be stored in the repeater syringe.

250 mL and 500 mL bottle sizes: Use only automatic syringe equipment provided by Boehringer Ingelheim Animal Health USA Inc. To obtain compatible equipment, contact Boehringer Ingelheim Animal Health USA Inc. at 1-888-637-4251 or your veterinarian. LONGRANGE should not be stored in automatic syringe equipment. Automatic syringe equipment should be thoroughly cleaned after each use. Discard bottle after one stopper puncture with draw-off spike.

Alternatively, a 50-mL polypropylene repeater syringe compatible with LONGRANGE may be used. To obtain a list of compatible equipment, contact Boehringer Ingelheim Animal Health USA Inc. at 1-888-637-4251. When using a repeater syringe, do not use beyond 3 months after stopper has been punctured. Discard bottle after 15 punctures. LONGRANGE should not be stored in the repeater syringe.

WARNINGS AND PRECAUTIONS

Withdrawal Periods and Residue Warnings

Animals intended for human consumption must not be slaughtered within 48 days of the last treatment.

This drug product is not approved for use in female dairy cattle 20 months of age or older, including dry dairy cows. Use in these cattle may cause drug residues in milk and/or in calves born to these cows.

A withdrawal period has not been established for pre-ruminating calves. Do not use in calves to be processed for veal.

User Safety Warnings

Not for Use in Humans. Keep this and all drugs out of the reach of children. Reproductive and developmental toxicities have been reported in laboratory animals following high, repeated exposures to N-methyl-2- pyrrolidone (NMP). Pregnant women should wear gloves and exercise caution or avoid handling this product. The Safety Data Sheet (SDS) contains more detailed occupational safety information.

To report adverse effects, to obtain an SDS, or for assistance, contact Boehringer Ingelheim Animal Health USA Inc. at 1-888-637-4251. For additional information about adverse drug experience reporting for animal drugs, contact FDA at 1-888-FDA-VETS or www.fda.gov/reportanimalae.

Animal Safety Warnings and Precautions

The product is likely to cause tissue damage at the site of injection, including possible granulomas and necrosis. These reactions have disappeared without treatment. Local tissue reaction may result in trim loss of edible tissue at slaughter.

Observe cattle for injection site reactions. If injection site reactions are suspected, consult your veterinarian. This product is not for intravenous or intramuscular use. Protect product from light. LONGRANGE (eprinomectin) has been developed specifically for use in cattle only. This product should not be used in other animal species.

When to Treat Cattle with Grubs

LONGRANGE effectively controls all stages of cattle grubs. However, proper timing of treatment is important. For the most effective results, cattle should be treated as soon as possible after the end of the heel fly (warble fly) season. Destruction of Hypoderma larvae (cattle grubs) at the period when these grubs are in vital areas may cause undesirable host-parasite reactions, including the possibility of fatalities. Killing Hypoderma lineatum when it is in the tissue surrounding the esophagus (gullet) may cause salivation and bloat; killing H. bovis when it is in the vertebral canal may cause staggering or paralysis. These reactions are not specific to treatment with LONGRANGE, but can occur with any successful treatment of grubs. Cattle should be treated either before or after these stages of grub development. Consult your veterinarian concerning the proper time for treatment.

Environmental Hazards

Studies indicate that when eprinomectin comes in contact with soil, it readily and tightly binds to the soil and becomes inactive over time. Free eprinomectin may adversely affect fish and certain aquatic organisms. Do not contaminate water by direct application or by improper disposal of drug containers. Dispose of containers in an approved landfill or by incineration.

As with other avermectins, eprinomectin is excreted in the dung of treated animals and can inhibit the reproduction and growth of pest and beneficial insects that use dung as a source of food and for reproduction. The magnitude and duration of such effects are species and life-cycle specific. When used according to label directions, the product is not expected to have an adverse impact on populations of dung-dependent insects.

Not for use in cattle managed in feedlots or under intensive rotational grazing because the environmental impact has not been evaluated for these scenarios.

Other Warnings: Parasite resistance may develop to any dewormer, and has been reported for most classes of dewormers.

Treatment with a dewormer used in conjunction with parasite management practices appropriate to the geographic area and the animal(s) to be treated may slow the development of parasite resistance.

Fecal examinations or other diagnostic tests and parasite management history should be used to determine if the product is appropriate for the herd, prior to the use of any dewormer. Following the use of any dewormer, effectiveness of treatment should be monitored (for example, with the use of a fecal egg count reduction test or another appropriate method).

A decrease in a drug’s effectiveness over time as calculated by fecal egg count reduction tests may indicate the development of resistance to the dewormer administered. Your parasite management plan should be adjusted accordingly based on regular monitoring.

Macrocyclic lactones provide prolonged drug exposure that may increase selection pressure for resistant parasites. This effect may be more pronounced in extended-release formulations.

CLINICAL PHARMACOLOGY

Due to its unique formulation characteristics, when LONGRANGE is injected subcutaneously in the shoulder area of cattle, a polymeric PLGA matrix is formed. The biodegradable matrix solidifies in vivo to form an in situ forming gel, which allows a gradual release of eprinomectin from the formulation. The rate-limiting step is diffusion of the drug through the gel matrix. Because of its mechanism of release, absorption characteristics can be highly dependent upon the injection technique used and the corresponding surface to volume ratio of the gel.

Clinical efficacy of avermectins and milbemycins is closely related to their pharmacokinetic behavior, and the time of parasite exposure to active drug concentrations is relevant to obtain optimal and persistent antiparasitic activity (Lanusse et al., 1997; Lifschitz et al., 1999; Lifschitz et al., 2004; Shoop et al., 1996). Lifschitz et al. (1999) indicated that plasma concentrations between 0.5 and 1 ng/mL would represent the minimal drug level required for optimal nematocidal activity, while others have suggested minimum levels of 1 to 2 ng/mL. Pharmacokinetic studies of LONGRANGE in cattle indicate that effective plasma levels remain for an extended period of time (at least 100 days).

Mean Eprinomectin B1a Plasma Concentration Versus Time Following a Single Subcutaneous Injection of LONGRANGE at a Dose Rate of 1 mg Eprinomectin per kg Body Weight in Beef Cattle

Mode of Action

The macrocyclic lactones have a unique mode of action. Compounds of this class bind selectively and with high affinity to glutamate-gated chloride ion channels that are present in invertebrate nerve and muscle cells. This leads to an increase in the permeability of the cell membrane to chloride ions with hyperpolarization of the nerve or muscle cell, resulting in paralysis and death of the parasite. Compounds of this class may also interact in other ligand-gated chloride ion channels, such as those gated by the neurotransmitter gamma-aminobutyric acid (GABA).

The margin of safety for compounds of this class is at least partially attributable to the fact that mammals do not have glutamate-gated chloride ion channels, and that the macrocyclic lactones have low affinity for other mammalian ligand-gated channels and do not readily cross the blood-brain barrier.

TARGET ANIMAL SAFETY

Clinical studies have demonstrated the wide margin of safety of LONGRANGE (eprinomectin). Overdosing at 3 to 5 times the recommended dose resulted in a statistically significant reduction in average weight gain when compared to the group tested at label dose. Treatment-related lesions observed in most cattle administered the product included swelling, hyperemia, or necrosis in the subcutaneous tissue of the skin. The administration of LONGRANGE at 3 times the recommended therapeutic dose had no adverse reproductive effects on beef cows at all stages of breeding or pregnancy or on their calves.

Not for use in bulls, as reproductive safety testing has not been conducted in males intended for breeding or actively breeding. Not for use in calves less than 3 months of age because safety testing has not been conducted in calves less than 3 months of age.

HOW SUPPLIED

LONGRANGE is available in three ready-to-use glass bottle sizes. The 100, 250 and 500 mL bottles contain sufficient solution to treat 20, 50 and 100 head of 550 lb (250 kg) cattle, respectively. The 250 and 500 mL bottles are supplied in a removable plastic protector.

STORAGE

Store at 77° F (25° C) with excursions between 59° and 86° F (15° and 30° C). Protect from light.

Approved by FDA under NADA # 141-327

Marketed by: Boehringer Ingelheim Animal Health USA Inc., Duluth, GA 30096

The Cattle Head Logo® and LONGRANGE® are registered trademarks of

Boehringer Ingelheim Animal Health USA Inc.

©2022 Boehringer Ingelheim Animal Health USA Inc. All rights reserved.

1050-2889-09, Rev. 07/2022 8LON016F

Principal Display Panel - 250 mL Display Carton - Front and Side Panel

LONGRANGE®
(eprinomectin)

5% Sterile Solution

Extended-Release Injectable
For Subcutaneous Use

Parasiticide for Cattle on Pasture

Caution: Federal law restricts this drug to use by or on
the order of a licensed veterinarian.

Approved by FDA under NADA # 141-327

250 mL